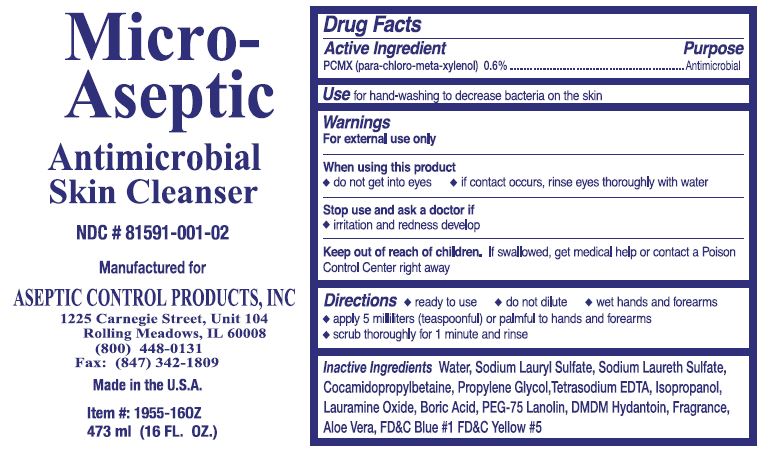 DRUG LABEL: Micro-Aseptic
NDC: 81591-001 | Form: LIQUID
Manufacturer: ASEPTIC CONTROL PRODUCTS, INC.
Category: otc | Type: HUMAN OTC DRUG LABEL
Date: 20241126

ACTIVE INGREDIENTS: CHLOROXYLENOL 0.6 g/100 mL
INACTIVE INGREDIENTS: WATER; FD&C BLUE NO. 1; ALOE VERA LEAF; FD&C YELLOW NO. 5; SODIUM LAURYL SULFATE; COCAMIDOPROPYL BETAINE; PROPYLENE GLYCOL; ISOPROPYL ALCOHOL; DMDM HYDANTOIN; PEG-75 LANOLIN; LAURAMINE OXIDE; SODIUM LAURETH SULFATE; EDETATE SODIUM; BORIC ACID

Micro-Aseptic 81591-001

Active Ingredient

PCMX (para-chloro-meta-xylenol) 0.6%

Purpose

Antimicrobial

Use

for hand-washing to decrease bacteria on the skin

Warnings

For external use only

When using this product

- do not get into eyes
- of contact occurs, rinse eyes thoroughly with water

Stop use and ask a doctor if

- irritation and redness develop

Keep out of reach of children.

If swallowed, get medical help or contact a Poison Control center right away

Directions

- ready to use
- do not dilute
- wet hands and forearms
- apply 5 milliters (teaspoonful) or palmful to hands and forearms
- scrub thoroughly for 1 minute and rinse

Inactive Ingredients

Water, Sodium Lauryl Sulfate, Sodium Laureth Sulfate, Cocamidopropylbetaine, Propylene Glycol, Tetrasodium EDTA, Isopropanol, Lauramine oxide, Boric Acid, PEG-75 Lanolin, DMDM Hydantoin, Fragrance, Aloe Vera, FD&C Blue #1, FD&C Yellow #5

PACKAGE LABEL

Micro-

Aseptic

Antimicrobial

Skin Cleanser

NDC # 81591-001-02

Manufactured for

ASEPTIC CONTROL PRODUCTS, INC

1225 Carnegie Street, Unit 104

Rolling Meadows, IL 60008

Made in the U.S.A.

Item #: 1955-16OZ

473 ml (16 FL. OZ.)